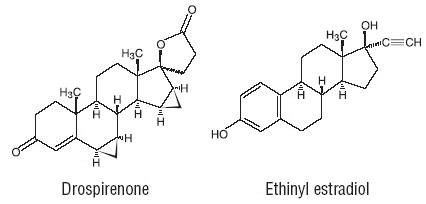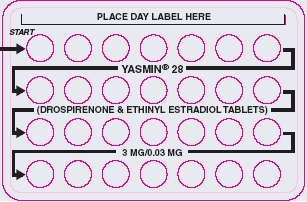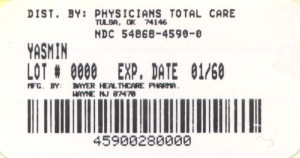 DRUG LABEL: Yasmin
NDC: 54868-4590 | Form: KIT | Route: ORAL
Manufacturer: Physicians Total Care, Inc.
Category: prescription | Type: HUMAN PRESCRIPTION DRUG LABEL
Date: 20120315

ACTIVE INGREDIENTS: DROSPIRENONE 3 mg/1 1; ETHINYL ESTRADIOL 0.03 mg/1 1
INACTIVE INGREDIENTS: STARCH, CORN; FERRIC OXIDE YELLOW; HYPROMELLOSES; LACTOSE MONOHYDRATE; POLYETHYLENE GLYCOL 6000; MAGNESIUM STEARATE; POVIDONE K25; TALC; TITANIUM DIOXIDE; STARCH, CORN; HYPROMELLOSES; LACTOSE MONOHYDRATE; MAGNESIUM STEARATE; POVIDONE K25; TALC; TITANIUM DIOXIDE

HIGHLIGHTS OF PRESCRIBING INFORMATION

These highlights do not include all the information needed to use YASMIN safely and effectively. See full prescribing information for YASMIN.
YASMIN (drospirenone/ethinyl estradiol) tablets, for oral use
Initial U.S. Approval: 2001

RECENT MAJOR CHANGES

Warnings and Precautions, Thromboembolic Disorders (5.1)2/2012

WARNING: CIGARETTE SMOKING AND SERIOUS CARDIOVASCULAR EVENTS

See full prescribing information for complete boxed warning.

- Women over 35 years old who smoke should not use Yasmin. (4)
- Cigarette smoking increases the risk of serious cardiovascular events from combination oral contraceptive (COC) use. (4)

1 INDICATIONS AND USAGE

Yasmin is an estrogen/progestin COC indicated for use by women to prevent pregnancy. (1)

2 DOSAGE AND ADMINISTRATION

- Take one tablet daily by mouth at the same time every day. (2.1)
- Tablets must be taken in the order directed on the blister pack. (2.1)

3 DOSAGE FORMS AND STRENGTHS

Yasmin consists of 28 film-coated, biconvex tablets in the following order (3):

- 21 yellow tablets, each containing 3 mg drospirenone (DRSP) and 0.03 mg ethinyl estradiol (EE),
- 7 inert white tablets

4 CONTRAINDICATIONS

- Renal impairment (4)
- Adrenal insufficiency (4)

- A high risk of arterial or venous thrombotic diseases (4)
- Undiagnosed abnormal uterine bleeding (4)
- Breast cancer or other estrogen- or progestin-sensitive cancer (4)
- Liver tumors or liver disease (4)
- Pregnancy (4)

5 WARNINGS AND PRECAUTIONS

- Vascular risks: Stop Yasmin if a thrombotic event occurs. Stop at least 4 weeks before and through 2 weeks after major surgery. Start no earlier than 4 weeks after delivery, in women who are not breastfeeding. (5.1)
- Hyperkalemia: DRSP has antimineralocorticoid activity. Do not use in patients predisposed to hyperkalemia. Check serum potassium concentration during the first treatment cycle in women on long-term treatment with medications that may increase serum potassium concentration. (5.2, 7.3)
- Liver disease: Discontinue Yasmin if jaundice occurs. (5.4)
- High blood pressure: Do not prescribe Yasmin for women with uncontrolled hypertension or hypertension with vascular disease. (5.5)
- Carbohydrate and lipid metabolic effects: Monitor prediabetic and diabetic women taking Yasmin. Consider an alternate contraceptive method for women with uncontrolled dyslipidemia. (5.7)
- Headache: Evaluate significant change in headaches and discontinue Yasmin if indicated. (5.8)
- Uterine bleeding: Evaluate irregular bleeding or amenorrhea. (5.9)

6 ADVERSE REACTIONS

The most frequent adverse reactions (≥ 2%) are premenstrual syndrome (13.2%), headache /migraine (10.7%), breast pain/tenderness/discomfort (8.3%), nausea/vomiting (4.5%), abdominal pain/tenderness/discomfort (2.3%), mood changes (2.3%). (6.1)

To report SUSPECTED ADVERSE REACTIONS, contact Bayer or FDA at 1-800-FDA-1088 or www.fda.gov/medwatch

7 DRUG INTERACTIONS

Drugs or herbal products that induce certain enzymes (for example, CYP3A4) may decrease the effectiveness of COCs or increase breakthrough bleeding. Counsel patients to use a back-up or alternative method of contraception when enzyme inducers are used with COCs. (7.1)

8 USE IN SPECIFIC POPULATIONS

Nursing mothers: Not recommended; can decrease milk production. (8.3)

FULL PRESCRIBING INFORMATION

WARNING: CIGARETTE SMOKING AND SERIOUS CARDIOVASCULAR EVENTS

Cigarette smoking increases the risk of serious cardiovascular events from combination oral contraceptives (COC) use. This risk increases with age, particularly in women over 35 years of age, and with the number of cigarettes smoked. For this reason, COCs should not be used by women who are over 35 years of age and smoke [see Contraindications (4)].

1 INDICATIONS AND USAGE

Yasmin is indicated for use by women to prevent pregnancy.

2 DOSAGE AND ADMINISTRATION

2.1 How to Take Yasmin

Take one tablet by mouth at the same time every day. The failure rate may increase when pills are missed or taken incorrectly.

To achieve maximum contraceptive effectiveness, Yasmin must be taken as directed, in the order directed on the blister pack.. Single missed pills should be taken as soon as remembered.

2.2 How to Start Yasmin

Instruct the patient to begin taking Yasmin either on the first day of her menstrual period (Day 1 Start) or on the first Sunday after the onset of her menstrual period (Sunday Start).

Day 1 Start

During the first cycle of Yasmin use, instruct the patient to take one yellow Yasmin daily, beginning on Day 1 of her menstrual cycle. (The first day of menstruation is Day 1.) She should take one yellow Yasmin daily for 21 consecutive days, followed by one white tablet daily on Days 22 through 28. Yasmin should be taken in the order directed on the package at the same time each day, preferably after the evening meal or at bedtime with some liquid, as needed. Yasmin can be taken without regard to meals. If Yasmin is first taken later than the first day of the menstrual cycle, Yasmin should not be considered effective as a contraceptive until after the first 7 consecutive days of product administration. Instruct the patient to use a non-hormonal contraceptive as back-up during the first 7 days. The possibility of ovulation and conception prior to initiation of medication should be considered.

Sunday Start

During the first cycle of Yasmin use, instruct the patient to take one yellow Yasmin daily, beginning on the first Sunday after the onset of her menstrual period. She should take one yellow Yasmin daily for 21 consecutive days, followed by one white tablet daily on Days 22 through 28. Yasmin should be taken in the order directed on the package at the same time each day, preferably after the evening meal or at bedtime with some liquid, as needed. Yasmin can be taken without regard to meals. Yasmin should not be considered effective as a contraceptive until after the first 7 consecutive days of product administration. Instruct the patient to use a non-hormonal contraceptive as back-up during the first 7 days. The possibility of ovulation and conception prior to initiation of medication should be considered.

The patient should begin her next and all subsequent 28-day regimens of Yasmin on the same day of the week that she began her first regimen, following the same schedule. She should begin taking her yellow tablets on the next day after ingestion of the last white tablet, regardless of whether or not a menstrual period has occurred or is still in progress. Anytime a subsequent cycle of Yasmin is started later than the day following administration of the last white tablet, the patient should use another method of contraception until she has taken a yellow Yasmin daily for seven consecutive days.

When switching from a different birth control pill

When switching from another birth control pill, Yasmin should be started on the same day that a new pack of the previous oral contraceptive would have been started.

When switching from a method other than a birth control pill

When switching from a transdermal patch or vaginal ring, Yasmin should be started when the next application would have been due. When switching from an injection, Yasmin should be started when the next dose would have been due. When switching from an intrauterine contraceptive or an implant, Yasmin should be started on the day of removal.

Withdrawal bleeding usually occurs within 3 days following the last yellow tablet. If spotting or breakthrough bleeding occurs while taking Yasmin, instruct the patient to continue taking Yasmin by the regimen described above. Counsel her that this type of bleeding is usually transient and without significance; however, advise her that if the bleeding is persistent or prolonged, she should consult her healthcare provider.

Although the occurrence of pregnancy is low if Yasmin is taken according to directions, if withdrawal bleeding does not occur, consider the possibility of pregnancy. If the patient has not adhered to the prescribed dosing schedule (missed one or more active tablets or started taking them on a day later than she should have), consider the possibility of pregnancy at the time of the first missed period and take appropriate diagnostic measures. If the patient has adhered to the prescribed regimen and misses two consecutive periods, rule out pregnancy. Discontinue Yasmin if pregnancy is confirmed.

The risk of pregnancy increases with each active yellow tablet missed. For additional patient instructions regarding missed pills, see the “WHAT TO DO IF YOU MISS PILLS” section in the FDA-Approved Patient Labeling. If breakthrough bleeding occurs following missed tablets, it will usually be transient and of no consequence. If the patient misses one or more white tablets, she should still be protected against pregnancy provided she begins taking a new cycle of yellow tablets on the proper day.

For postpartum women who do not breastfeed or after a second trimester abortion, start Yasmin no earlier than 4 weeks postpartum due to the increased risk of thromboembolism. If the patient starts Yasmin postpartum and has not yet had a period, evaluate for possible pregnancy, and instruct her to use an additional method of contraception until she has taken Yasmin for 7 consecutive days.

2.3 Advice in Case of Gastrointestinal Disturbances

In case of severe vomiting or diarrhea, absorption may not be complete and additional contraceptive measures should be taken. If vomiting occurs within 3-4 hours after tablet-taking, this can be regarded as a missed tablet.

3 DOSAGE FORMS AND STRENGTHS

Yasmin (drospirenone/ethinyl estradiol) tablets are available in blister packs.

Each blister pack contains 28 film-coated, round, bi-convex tablets in the following order:

- 21 yellow tablets each containing 3 mg drospirenone (DRSP) and 0.03 mg ethinyl estradiol (EE) embossed with a “DO” in a regular hexagon on one side
- 7 inert white tablets embossed with a “DP” in a regular hexagon on one side

4 CONTRAINDICATIONS

Do not prescribe Yasmin to women who are known to have the following:

- Renal impairment
- Adrenal insufficiency
- A high risk of arterial or venous thrombotic diseases. Examples include women who are known to:
  - Smoke, if over age 35 [see Boxed Warning and Warnings and Precautions (5.1)]
  - Have deep vein thrombosis or pulmonary embolism, now or in the past [see Warnings and Precautions (5.1)]
- Have cerebrovascular disease [see Warnings and Precautions (5.1)]
- Have coronary artery disease [see Warnings and Precautions (5.1)]
- Have thrombogenic valvular or thrombogenic rhythm diseases of the heart (for example, subacute bacterial endocarditis with valvular disease, or atrial fibrillation) [see Warnings and Precautions (5.1)]
- Have inherited or acquired hypercoagulopathies [see Warnings and Precautions (5.1)]
- Have uncontrolled hypertension [see Warnings and Precautions (5.5)]
- Have diabetes mellitus with vascular disease [see Warnings and Precautions (5.7)]
- Have headaches with focal neurological symptoms or have migraine headaches with or without aura if over age 35 [see Warnings and Precautions (5.8)]
- Undiagnosed abnormal uterine bleeding [see Warnings and Precautions (5.9)]
- Breast cancer or other estrogen- or progestin-sensitive cancer, now or in the past [see Warnings and Precautions (5.3)]
- Liver tumor (benign or malignant) or liver disease [see Warnings and Precautions (5.4) and Use in Specific Populations (8.7)]
- Pregnancy, because there is no reason to use COCs during pregnancy [see Warnings and Precautions (5.10) and Use in Specific Populations (8.1)]

5 WARNINGS AND PRECAUTIONS

5.1 Thromboembolic Disorders and Other Vascular Problems

Stop Yasmin if an arterial or venous thrombotic (VTE) event occurs.

The use of COCs increases the risk of venous thromboembolism. However, pregnancy increases the risk of venous thromboembolism as much or more than the use of COCs. The risk of VTE in women using COCs has been estimated to be 3 to 9 per 10,000 woman-years. The risk of VTE is highest during the first year of use. Data from a large, prospective cohort safety study of various COCs suggest that this increased risk, as compared to that in non-COC users, is greatest during the first 6 months of COC use. Data from this safety study indicate that the greatest risk of VTE is present after initially starting a COC or restarting (following a 4 week or greater pill-free interval) the same or a different COC.

Use of COCs also increases the risk of arterial thromboses such as strokes and myocardial infarctions, especially in women with other risk factors for these events.

The risk of thromboembolic disease due to oral contraceptives gradually disappears after COC use is discontinued.

If feasible, stop Yasmin at least 4 weeks before and through 2 weeks after major surgery or other surgeries known to have an elevated risk of thromboembolism.

Start Yasmin no earlier than 4 weeks after delivery, in women who are not breastfeeding. The risk of postpartum thromboembolism decreases after the third postpartum week, whereas the risk of ovulation increases after the third postpartum week.

COCs have been shown to increase both the relative and attributable risks of cerebrovascular events (thrombotic and hemorrhagic strokes), although, in general, the risk is greatest among older (35 years of age), hypertensive women who also smoke. COCs also increase the risk for stroke in women with other underlying risk factors.

Oral contraceptives must be used with caution in women with cardiovascular disease risk factors.

Stop Yasmin if there is unexplained loss of vision, proptosis, diplopia, papilledema, or retinal vascular lesions. Evaluate for retinal vein thrombosis immediately.

Epidemiologic studies including a DRSP-containing COC

Several studies have investigated the relative risks of thromboembolism in women using Yasmin compared to those in women using COCs containing other progestins. Two prospective cohort studies, both evaluating the risk of venous and arterial thromboembolism and death, were initiated at the time of Yasmin approval.^1,2 The first (EURAS) showed the risk of thromboembolism (particularly venous thromboembolism) and death in Yasmin users to be comparable to that of other oral contraceptive preparations, including those containing levonorgestrel (a so-called second generation COC). The second prospective cohort study (Ingenix) also showed a comparable risk of thromboembolism in Yasmin users compared to users of other COCs, including those containing levonorgestrel. In the second study, COC comparator groups were selected based on their having similar characteristics to those being prescribed Yasmin.

Two additional epidemiological studies, one case-control study (van Hylckama Vlieg et al. ^3) and one retrospective cohort study (Lidegaard et al. ^4) suggested that the risk of venous thromboembolism occurring in Yasmin users was higher than that for users of levonorgestrel-containing COCs and lower than that for users of desogestrel/gestodene-containing COCs (so-called third generation COCs). In the case-control study, however, the number of Yasmin cases was very small (1.2% of all cases) making the risk estimates unreliable. The relative risk for Yasmin users in the retrospective cohort study was greater than that for users of other COC products when considering women who used the products for less than one year. However, these one-year estimates may not be reliable because the analysis may include women of varying risk levels. Among women who used the product for 1 to 4 years, the relative risk was similar for users of Yasmin to that for users of other COC products.

5.2 Hyperkalemia

Yasmin contains 3 mg of the progestin DRSP, which has antimineralocorticoid activity, including the potential for hyperkalemia in high-risk patients, comparable to a 25 mg dose of spironolactone. Yasmin should not be used in patients with conditions that predispose to hyperkalemia (that is, renal impairment, hepatic impairment, and adrenal insufficiency). Women receiving daily, long-term treatment for chronic conditions or diseases with medications that may increase serum potassium concentration should have their serum potassium concentration checked during the first treatment cycle. Medications that may increase serum potassium concentration include ACE inhibitors, angiotensin–II receptor antagonists, potassium-sparing diuretics, potassium supplementation, heparin, aldosterone antagonists, and NSAIDs.

5.3 Carcinoma of the Breasts and Reproductive Organs

Women who currently have or have had breast cancer should not use Yasmin because breast cancer is a hormonally-sensitive tumor.

There is substantial evidence that COCs do not increase the incidence of breast cancer. Although some past studies have suggested that COCs might increase the incidence of breast cancer, more recent studies have not confirmed such findings.

Some studies suggest that COCs are associated with an increase in the risk of cervical cancer or intraepithelial neoplasia. However, there is controversy about the extent to which these findings may be due to differences in sexual behavior and other factors.

5.4 Liver Disease

Discontinue Yasmin if jaundice develops. Steroid hormones may be poorly metabolized in patients with impaired liver function. Acute or chronic disturbances of liver function may necessitate the discontinuation of COC use until markers of liver function return to normal and COC causation has been excluded.

Hepatic adenomas are associated with COC use. An estimate of the attributable risk is 3.3 cases/100,000 COC users. Rupture of hepatic adenomas may cause death through intra-abdominal hemorrhage.

Studies have shown an increased risk of developing hepatocellular carcinoma in long-term (8 years) COC users. However, the attributable risk of liver cancers in COC users is less than one case per million users.

Oral contraceptive-related cholestasis may occur in women with a history of pregnancy-related cholestasis. Women with a history of COC-related cholestasis may have the condition recur with subsequent COC use.

5.5 High Blood Pressure

For women with well-controlled hypertension, monitor blood pressure and stop Yasmin if blood pressure rises significantly. Women with uncontrolled hypertension or hypertension with vascular disease should not use COCs.

An increase in blood pressure has been reported in women taking COCs, and this increase is more likely in older women and with extended duration of use. The incidence of hypertension increases with increasing concentration of progestin.

5.6 Gallbladder Disease

Studies suggest a small increased relative risk of developing gallbladder disease among COC users.

5.7 Carbohydrate and Lipid Metabolic Effects

Carefully monitor prediabetic and diabetic women who are taking Yasmin. COCs may decrease glucose tolerance in a dose-related fashion.

Consider alternative contraception for women with uncontrolled dyslipidemia. A small proportion of women will have adverse lipid changes while on COCs.

Women with hypertriglyceridemia, or a family history thereof, may be at an increased risk of pancreatitis when using COCs.

5.8 Headache

If a woman taking Yasmin develops new headaches that are recurrent, persistent, or severe, evaluate the cause and discontinue Yasmin if indicated.

An increase in frequency or severity of migraine during COC use (which may be prodromal of a cerebrovascular event) may be a reason for immediate discontinuation of the COC.

5.9 Bleeding Irregularities

Unscheduled (breakthrough or intracyclic) bleeding and spotting sometimes occur in patients on COCs, especially during the first three months of use. If bleeding persists or occurs after previously regular cycles, check for causes such as pregnancy or malignancy. If pathology and pregnancy are excluded, bleeding irregularities may resolve over time or with a change to a different COC.

Data from ten contraceptive efficacy clinical trials (N=2,467) show that the percent of women who took Yasmin and experienced unscheduled bleeding decreased over time from 12% at cycle 2 to 6% (cycle 13). A total of 24 subjects out of 2,837 in the Yasmin trials (<1%) discontinued due to bleeding complaints. These are described as metrorrhagia, vaginal hemorrhage, menorrhagia, abnormal withdrawal bleeding, and menometrorrhagia.

The average duration of scheduled bleeding episodes in the majority of subjects (86%-88%) was 4-7 days. Women who use Yasmin may experience absence of withdrawal bleeding, even if they are not pregnant. Based on subject diaries from contraceptive efficacy trials, during cycles 2–13, 1-11% of women per cycle experienced no withdrawal bleeding. Some women may encounter post-pill amenorrhea or oligomenorrhea, especially when such a condition was pre-existent.

If withdrawal bleeding does not occur, consider the possibility of pregnancy. If the patient has not adhered to the prescribed dosing schedule (missed one or more active tablets or started taking them on a day later than she should have), consider the possibility of pregnancy at the time of the first missed period and take appropriate diagnostic measures. If the patient has adhered to the prescribed regimen and misses two consecutive periods, rule out pregnancy.

5.10 COC Use Before or During Early Pregnancy

Extensive epidemiological studies have revealed no increased risk of birth defects in women who have used oral contraceptives prior to pregnancy. Studies also do not suggest a teratogenic effect when COCs are taken inadvertently during early pregnancy, particularly in so far as cardiac anomalies and limb-reduction defects are concerned.

The administration of oral contraceptives to induce withdrawal bleeding should not be used as a test for pregnancy [see Use in Specific Populations (8.1)].

5.11 Depression

Women with a history of depression should be carefully observed and Yasmin discontinued if depression recurs to a serious degree.

5.12 Interference with Laboratory Tests

1. The use of COCs may change the results of some laboratory tests, such as coagulation factors, lipids, glucose tolerance, and binding proteins. Women on thyroid hormone replacement therapy may need increased doses of thyroid hormone because serum concentrations of thyroid-binding globulin increase with use of COCs [see Drug Interactions (7.2)].
2. DRSP causes an increase in plasma renin activity and plasma aldosterone induced by its mild antimineralocorticoid activity.

5.13 Monitoring

A woman who is taking COCs should have a yearly visit with her healthcare provider for a blood pressure check and for other indicated healthcare.

5.14 Other Conditions

In women with hereditary angioedema, exogenous estrogens may induce or exacerbate symptoms of angioedema. Chloasma may occasionally occur, especially in women with a history of chloasma gravidarum. Women with a tendency to chloasma should avoid exposure to the sun or ultraviolet radiation while taking COCs.

6 ADVERSE REACTIONS

The following serious adverse reactions with the use of COCs are discussed elsewhere in the labeling:

- Serious cardiovascular events and stroke[see Boxed Warning and Warnings and Precautions (5.1)]
- Vascular events [see Warnings and Precautions (5.1)]
- Liver disease [see Warnings and Precautions (5.4)]

Adverse reactions commonly reported by COC users are:

- Irregular uterine bleeding
- Nausea
- Breast tenderness
- Headache

6.1 Clinical Trials Experience

Because clinical trials are conducted under widely varying conditions, the adverse reaction rates observed cannot be directly compared to rates in other clinical trials and may not reflect the rates observed in practice.

The data provided reflect the experience with the use of Yasmin (3 mg DRSP/0.03 mg EE) in the adequate and well-controlled studies for contraception (N=2,837). The US pivotal clinical study (N=326) was a multicenter, open-label trial in healthy women aged 18 -35 who were treated for up to 13 cycles. The second pivotal study (N=442)was a multicenter, randomized, open-label comparative European study of Yasmin vs. 0.150 mg desogestrel/0.03 mg EE conducted in healthy women aged 17-40 who were treated for up to 26 cycles.

The most common adverse reactions (≥ 2% of users) were: premenstrual syndrome (13.2%), headache/migraine (10.7%), breast pain/tenderness/discomfort (8.3%), nausea/vomiting (4.5%) abdominal pain/discomfort/tenderness (2.3%) and mood changes (depression, depressed mood, irritability, mood swings, mood altered and affect lability (2.3%).

Adverse Reactions (≥ 1%) Leading to Study Discontinuation:

Of 2,837 women, 6.7% discontinued from the clinical trials due to an adverse reaction; the most frequent adverse reaction leading to discontinuation was headache/migraine (1.5%).

Serious Adverse Reactions:

Depression, pulmonary embolism, toxic skin eruption, and uterine leiomyoma.

6.2 Postmarketing Experience

The following adverse reactions have been identified during post-approval use of Yasmin. Because these reactions are reported voluntarily from a population of uncertain size, it is not always possible to reliably estimate their frequency or establish a causal relationship to drug exposure.

Adverse reactions, including fatalities, are grouped into System Organ Classes and ordered by frequency.

Vascular disorders: Venous and arterial thromboembolic events (including pulmonary emboli, deep vein thrombosis, intracardiac thrombosis, intracranial venous sinus thrombosis, sagittal sinus thrombosis, retinal vein occlusion, myocardial infarction and stroke), hypertension

Hepatobiliary disorders: Gallbladder disease

Immune system disorders: Hypersensitivity

Metabolism and nutrition disorders: Hyperkalemia

Skin and subcutaneous tissue disorders: Chloasma

7 DRUG INTERACTIONS

Consult the labeling of all concurrently-used drugs to obtain further information about interactions with hormonal contraceptives or the potential for enzyme alterations.

7.1 Effects of Other Drugs on Combined Oral Contraceptives

Substances diminishing the efficacy of COCs: Drugs or herbal products that induce certain enzymes, including cytochrome P450 3A4 (CYP3A4), may decrease the effectiveness of COCs or increase breakthrough bleeding. Some drugs or herbal products that may decrease the effectiveness of hormonal contraceptives include phenytoin, barbiturates, carbamazepine, bosentan, felbamate, griseofulvin, oxcarbazepine, rifampicin, topiramate and products containing St. John’s wort. Interactions between oral contraceptives and other drugs may lead to breakthrough bleeding and/or contraceptive failure. Counsel women to use an alternative method of contraception or a back-up method when enzyme inducers are used with COCs, and to continue back-up contraception for 28 days after discontinuing the enzyme inducer to ensure contraceptive reliability.

Substances increasing the plasma concentrations of COCs:Co-administration of atorvastatin with certain COCs containing EE increase AUC values for EE by approximately 20%. Ascorbic acid and acetaminophen may increase plasma EE concentrations, possibly by inhibition of conjugation. CYP3A4 inhibitors such as itraconazole or ketoconazole may increase plasma hormone concentrations.

Human immunodeficiency virus (HIV)/Hepatitis C virus (HCV) protease inhibitors and non-nucleoside reverse transcriptase inhibitors: Significant changes (increase or decrease) in the plasma concentrations of estrogen and progestin have been noted in some cases of co-administration with HIV/HCV protease inhibitors or with non-nucleoside reverse transcriptase inhibitors.

Antibiotics: There have been reports of pregnancy while taking hormonal contraceptives and antibiotics, but clinical pharmacokinetic studies have not shown consistent effects of antibiotics on plasma concentrations of synthetic steroids.

Effect on DRSP: The main metabolites of DRSP in human plasma are generated without involvement of the CYP system. Inhibitors of this enzyme system are therefore unlikely to influence the metabolism of DRSP.

7.2 Effects of Combined Oral Contraceptives on Other Drugs

COCs containing EE may inhibit the metabolism of other compounds. COCs have been shown to significantly decrease plasma concentrations of lamotrigine, likely due to induction of lamotrigine glucuronidation. This may reduce seizure control; therefore, dosage adjustments of lamotrigine may be necessary. Consult the labeling of the concurrently-used drug to obtain further information about interactions with COCs or the potential for enzyme alterations.

In vitro and clinical studies did not indicate an inhibitory potential of DRSP towards human CYP enzymes at clinically relevant concentrations [see Clinical Pharmacology (12.3)].

Women on thyroid hormone replacement therapy may need increased doses of thyroid hormone because serum concentration of thyroid-binding globulin increases with use of COCs.

Potential to Increase Serum Potassium Concentration: There is a potential for an increase in serum potassium concentration in women taking Yasmin with other drugs that may increase serum potassium concentration [see Warnings and Precautions (5.2) and Clinical Pharmacology (12.3)].

7.3 Interference with Laboratory Tests

1. The use of contraceptive steroids may influence the results of certain laboratory tests, such as coagulation factors, lipids, glucose tolerance, and binding proteins. DRSP causes an increase in plasma renin activity and plasma aldosterone induced by its mild antimineralocorticoid activity[see Warnings and Precautions (5.12) and Drug Interactions (7.2)].

8 USE IN SPECIFIC POPULATIONS

8.1 Pregnancy

There is little or no increased risk of birth defects in women who inadvertently use COCs during early pregnancy. Epidemiologic studies and meta-analyses have not found an increased risk of genital or non-genital birth defects (including cardiac anomalies and limb-reduction defects) following exposure to low dose COCs prior to conception or during early pregnancy.

The administration of COCs to induce withdrawal bleeding should not be used as a test for pregnancy. COCs should not be used during pregnancy to treat threatened or habitual abortion.

Women who do not breastfeed may start COCs no earlier than four weeks postpartum.

8.3 Nursing Mothers

When possible, advise the nursing mother to use other forms of contraception until she has weaned her child. Estrogen-containing COCs can reduce milk production in breastfeeding mothers. This is less likely to occur once breastfeeding is well-established; however, it can occur at any time in some women. Small amounts of oral contraceptive steroids and/or metabolites are present in breast milk.

After oral administration of Yasmin, about 0.02% of the DRSP dose was excreted into the breast milk of postpartum women within 24 hours. This results in a maximal daily dose of about 0.003 mg DRSP in an infant.

8.4 Pediatric Use

Safety and efficacy of Yasmin has been established in women of reproductive age. Efficacy is expected to be the same for postpubertal adolescents under the age of 18 and for users 18 years and older. Use of this product before menarche is not indicated.

8.5 Geriatric Use

Yasmin has not been studied in postmenopausal women and is not indicated in this population.

8.6 Patients with Renal Impairment

Yasmin is contraindicated in patients with renal impairment [see Contraindications (4) and Warnings and Precautions (5.2)].

In subjects with creatinine clearance (CLcr) of 50–79 mL/min, serum DRSP concentrations were comparable to those in a control group with CLcr ≥ 80 mL/min. In subjects with CLcr of 30–49 mL/min, serum DRSP concentrations were on average 37% higher than those in the control group. In addition, there is a potential to develop hyperkalemia in subjects with renal impairment whose serum potassium is in the upper reference range, and who are concomitantly using potassium sparing drugs [see Clinical Pharmacology (12.3)].

8.7 Patients with Hepatic Impairment

Yasmin is contraindicated in patients with hepatic disease [see Contraindications (4) and Warnings and Precautions (5.4)]. The mean exposure to DRSP in women with moderate liver impairment is approximately three times higher than the exposure in women with normal liver function. Yasmin has not been studied in women with severe hepatic impairment.

8.8 Race

No clinically significant difference was observed between the pharmacokinetics of DRSP or EE in Japanese versus Caucasian women [see Clinical Pharmacology (12.3)].

10 OVERDOSAGE

There have been no reports of serious ill effects from overdose, including ingestion by children. Overdosage may cause withdrawal bleeding in females and nausea.

DRSP is a spironolactone analogue which has antimineralocorticoid properties. Serum concentration of potassium and sodium, and evidence of metabolic acidosis, should be monitored in cases of overdose.

11 DESCRIPTION

Yasmin (drospirenone/ethinyl estradiol) tablets provide an oral contraceptive regimen consisting of 28 film-coated tablets that contain the ingredients specified for each tablet below:

- 21 yellow tablets each containing 3 mg DRSP and 0.03 mg EE
- 7 inert white tablets

The inactive ingredients in the yellow tablets are lactose monohydrate NF, corn starch NF, pregelatinized starch NF, povidone 25000 NF, magnesium stearate NF, hypromellose USP, macrogol 6000 NF, titanium dioxide USP, talc USP, and ferric oxide pigment, yellow NF. The white inert film-coated tablets contain lactose monohydrate NF, corn starch NF, povidone 25000 NF, magnesium stearate NF, hypromellose USP, talc USP, and titanium dioxide USP.

Drospirenone (6R,7R,8R,9S,10R,13S,14S,15S,16S,17S)-1,3',4',6,6a,7,8,9,10,11,12,13, 14,15,15a,16-hexadecahydro-10,13-dimethylspiro-[17H-dicyclopropa-[6,7:15,16] cyclopenta[a]phenanthrene-17,2'(5H)-furan]-3,5'(2H)-dione) is a synthetic progestational compound and has a molecular weight of 366.5 and a molecular formula of C24H30O3.

Ethinyl estradiol (19-nor-17α-pregna 1,3,5(10)-triene-20-yne-3,17-diol) is a synthetic estrogenic compound and has a molecular weight of 296.4 and a molecular formula of C20H24O2.

The structural formulas are as follows:

12 CLINICAL PHARMACOLOGY

12.1 Mechanism of Action

COCs lower the risk of becoming pregnant primarily by suppressing ovulation. Other possible mechanisms may include cervical mucus changes that inhibit sperm penetration and endometrial changes that reduce the likelihood of implantation.

12.2 Pharmacodynamics

Drospirenone is a spironolactone analogue with antimineralocorticoid activity. The estrogen in Yasmin is ethinyl estradiol (EE).

No specific pharmacodynamic studies were conducted with Yasmin.

12.3 Pharmacokinetics

Absorption

The absolute bioavailability of DRSP from a single entity tablet is about 76%. The absolute bioavailability of EE is approximately 40% as a result of presystemic conjugation and first-pass metabolism. The absolute bioavailability of Yasmin, which is a combination tablet of DRSP and EE, has not been evaluated. Serum concentrations of DRSP and EE reached peak levels within 1-2 hours after administration of Yasmin.

The pharmacokinetics of DRSP are dose proportional following single doses ranging from 1-10 mg. Following daily dosing of Yasmin, steady state DRSP concentrations were observed after 8 days. There was about 2 to 3 fold accumulation in serum Cmax and AUC (0-24h) values of DRSP following multiple dose administration of Yasmin (see Table 1).

For EE, steady-state conditions are reported during the second half of a treatment cycle. Following daily administration of Yasmin serum Cmax and AUC (0-24h) values of EE accumulate by a factor of about 1.5 to 2 (see Table 1).

Table 1 MEAN PHARMACOKINETIC PARAMETERS OF YASMIN

(DRSP 3 mg and EE 0.03 mg)
DRSP
Mean (%CV) Values
Cycle / Day | No. of Subjects | Cmax (ng/mL) | Tmax (h) | AUC(0-24h) (ng•h/mL) | t1/2 (h)
1/1 | 12 | 36.9 (13) | 1.7 (47) | 288 (25) | NA
1/21 | 12 | 87.5 (59) | 1.7 (20) | 827 (23) | 30.9 (44)
6/21 | 12 | 84.2 (19) | 1.8 (19) | 930 (19) | 32.5 (38)
9/21 | 12 | 81.3 (19) | 1.6 (38) | 957 (23) | 31.4 (39)
13/21 | 12 | 78.7 (18) | 1.6 (26) | 968 (24) | 31.1 (36)
EE
Mean (%CV) Values
Cycle / Day | No. of Subjects | Cmax (pg/mL) | Tmax (h) | AUC(0-24h) (pg•h/mL) | t1/2 (h)
1/1 | 11 | 53.5 (43) | 1.9 (45) | 280 (87) | NA
1/21 | 11 | 92.1 (35) | 1.5 (40) | 461 (94) | NA
6/21 | 11 | 99.1 (45) | 1.5 (47) | 346 (74) | NA
9/21 | 11 | 87 (43) | 1.5 (42) | 485 (92) | NA
13/21 | 10 | 90.5 (45) | 1.6 (38) | 469 (83) | NA

Food Effect

The rate of absorption of DRSP and EE following single administration of a formulation similar to Yasmin was slower under fed (high fat meal) conditions with the serum Cmax being reduced about 40% for both components. The extent of absorption of DRSP, however, remained unchanged. In contrast, the extent of absorption of EE was reduced by about 20% under fed conditions.

Distribution

DRSP and EE serum concentrations decline in two phases. The apparent volume of distribution of DRSP is approximately 4 L/kg and that of EE is reported to be approximately 4–5 L/kg.

DRSP does not bind to sex hormone binding globulin (SHBG) or corticosteroid binding globulin (CBG) but binds about 97% to other serum proteins. Multiple dosing over 3 cycles resulted in no change in the free fraction (as measured at trough concentrations). EE is reported to be highly but non-specifically bound to serum albumin (approximately 98.5 %) and induces an increase in the serum concentrations of both SHBG and CBG. EE induced effects on SHBG and CBG were not affected by variation of the DRSP dosage in the range of 2 to 3 mg.

Metabolism

The two main metabolites of DRSP found in human plasma were identified to be the acid form of DRSP generated by opening of the lactone ring and the 4,5-dihydrodrospirenone-3-sulfate. These metabolites were shown not to be pharmacologically active. In in vitro studies with human liver microsomes, DRSP was metabolized only to a minor extent mainly by CYP3A4.

EE has been reported to be subject to presystemic conjugation in both small bowel mucosa and the liver. Metabolism occurs primarily by aromatic hydroxylation but a wide variety of hydroxylated and methylated metabolites are formed. These are present as free metabolites and as conjugates with glucuronide and sulfate. CYP3A4 in the liver is responsible for the 2-hydroxylation which is the major oxidative reaction. The 2-hydroxy metabolite is further transformed by methylation and glucuronidation prior to urinary and fecal excretion.

Excretion

DRSP serum concentrations are characterized by a terminal disposition phase half-life of approximately 30 hours after both single and multiple dose regimens. Excretion of DRSP was nearly complete after ten days and amounts excreted were slightly higher in feces compared to urine. DRSP was extensively metabolized and only trace amounts of unchanged DRSP were excreted in urine and feces. At least 20 different metabolites were observed in urine and feces. About 38-47% of the metabolites in urine were glucuronide and sulfate conjugates. In feces, about 17-20% of the metabolites were excreted as glucuronides and sulfates.

For EE the terminal disposition phase half-life has been reported to be approximately 24 hours. EE is not excreted unchanged. EE is excreted in the urine and feces as glucuronide and sulfate conjugates and undergoes enterohepatic circulation.

Use in Specific Populations

Pediatric Use: Safety and efficacy of Yasmin has been established in women of reproductive age. Efficacy is expected to be the same for postpubertal adolescents under the age of 18 and for users 18 years and older. Use of this product before menarche is not indicated.

Geriatric Use: Yasmin has not been studied in postmenopausal women and is not indicated in this population.

Race: No clinically significant difference was observed between the pharmacokinetics of DRSP or EE in Japanese versus Caucasian women (age 25-35) when 3 mg DRSP/0.02 mg EE was administered daily for 21 days. Other ethnic groups have not been specifically studied.

Renal Impairment: Yasmin is contraindicated in patients with renal impairment.

The effect of renal impairment on the pharmacokinetics of DRSP (3 mg daily for 14 days) and the effect of DRSP on serum potassium concentrations were investigated in three separate groups of female subjects (n=28, age 30-65). All subjects were on a low potassium diet. During the study, 7 subjects continued the use of potassium-sparing drugs for the treatment of their underlying illness. On the 14th day (steady-state) of DRSP treatment, the serum DRSP concentrations in the group with CLcr of 50–79 mL/min were comparable to those in a control group with CLcr ≥ 80 mL/min. The serum DRSP concentrations were on average 37% higher in the group with CLcr of 30–49 mL/min compared to those in the control group. DRSP treatment did not show any clinically significant effect on serum potassium concentration. Although hyperkalemia was not observed in the study, in five of the seven subjects who continued use of potassium sparing drugs during the study, mean serum potassium concentrations increased by up to 0.33 mEq/L. [See Contraindications (4) and Warnings and Precautions (5.2).]

Hepatic Impairment: Yasmin is contraindicated in patients with hepatic disease.

The mean exposure to DRSP in women with moderate liver impairment is approximately three times higher than the exposure in women with normal liver function. Yasmin has not been studied in women with severe hepatic impairment [see Contraindications (4) and Warnings and Precautions (5.4)].

Drug Interactions

Consult the labeling of all concurrently used drugs to obtain further information about interactions with oral contraceptives or the potential for enzyme alterations.

Effects of Other Drugs on Combined Oral Contraceptives

Substances diminishing the efficacy of COCs: Drugs or herbal products that induce certain enzymes, including CYP3A4, may decrease the effectiveness of COCs or increase breakthrough bleeding.

Substances increasing the plasma concentrations of COCs: Co-administration of atorvastatin with certain COCs containing ethinyl estradiol increase AUC values for ethinyl estradiol by approximately 20%. Ascorbic acid and acetaminophen may increase plasma ethinyl estradiol concentrations, possibly by inhibition of conjugation. CYP3A4 inhibitors such as itraconazole or ketoconazole may increase plasma hormone concentrations.

HIV/HCV protease inhibitors and non-nucleoside reverse transcriptase inhibitors: Significant changes (increase or decrease) in the plasma concentrations of estrogen and progestin have been noted in some cases of co-administration with HIV/HCV protease inhibitors or with non-nucleoside reverse transcriptase inhibitors.

Antibiotics: There have been reports of pregnancy while taking hormonal contraceptives and antibiotics, but clinical pharmacokinetic studies have not shown consistent effects of antibiotics on plasma concentrations of synthetic steroids.

Effects of Combined Oral Contraceptives on Other Drugs

COCs containing ethinyl estradiol may inhibit the metabolism of other compounds. COCs have been shown to significantly decrease plasma concentrations of lamotrigine, likely due to induction of lamotrigine glucuronidation. This may reduce seizure control; therefore, dosage adjustments of lamotrigine may be necessary. Consult the labeling of the concurrently-used drug to obtain further information about interactions with COCs or the potential for enzyme alterations.

Metabolism of DRSP and potential effects of DRSP on hepatic CYP enzymes have been investigated in in vitro and in vivo studies. In in vitro studies DRSP did not affect turnover of model substrates of CYP1A2 and CYP2D6, but had an inhibitory influence on the turnover of model substrates of CYP1A1, CYP2C9, CYP2C19 and CYP3A4, with CYP2C19 being the most sensitive enzyme. The potential effect of DRSP on CYP2C19 activity was investigated in a clinical pharmacokinetic study using omeprazole as a marker substrate. In the study with 24 postmenopausal women [including 12 women with homozygous (wild type) CYP2C19 genotype and 12 women with heterozygous CYP2C19 genotype] the daily oral administration of 3 mg DRSP for 14 days did not affect the oral clearance of omeprazole (40 mg, single oral dose) and the CYP2C19 product 5-hydroxy omeprazole. Furthermore, no significant effect of DRSP on the systemic clearance of the CYP3A4 product omeprazole sulfone was found. These results demonstrate that DRSP did not inhibit CYP2C19 and CYP3A4 in vivo.

Two additional clinical drug-drug interaction studies using simvastatin and midazolam as marker substrates for CYP3A4 were each performed in 24 healthy postmenopausal women. The results of these studies demonstrated that pharmacokinetics of the CYP3A4 substrates were not influenced by steady state DRSP concentrations achieved after administration of 3 mg DRSP/day.

Women on thyroid hormone replacement therapy may need increased doses of thyroid hormone because serum concentration of thyroid-binding globulin increases with use of COCs.

Interactions With Drugs That Have the Potential to Increase Serum Potassium Concentration: There is a potential for an increase in serum potassium concentration in women taking Yasmin with other drugs that may increase serum potassium concentration [see Warnings and Precautions (5.2)].

A drug-drug interaction study of DRSP 3 mg/estradiol (E2) 1 mg versus placebo was performed in 24 mildly hypertensive postmenopausal women taking enalapril maleate 10 mg twice daily. Potassium concentrations were obtained every other day for a total of 2 weeks in all subjects. Mean serum potassium concentrations in the DRSP/E2 treatment group relative to baseline were 0.22 mEq/L higher than those in the placebo group. Serum potassium concentrations also were measured at multiple time points over 24 hours at baseline and on Day 14. On Day 14, the ratios for serum potassium Cmax and AUC in the DRSP/E2 group to those in the placebo group were 0.955 (90% CI: 0.914, 0.999) and 1.010 (90% CI: 0.944, 1.08), respectively. No patient in either treatment group developed hyperkalemia (serum potassium concentrations 5.5 mEq/L).

13 NONCLINICAL TOXICOLOGY

13.1 Carcinogenesis, Mutagenesis, Impairment of Fertility

In a 24 month oral carcinogenicity study in mice dosed with 10 mg/kg/day DRSP alone or 1 + 0.01, 3 + 0.03 and 10 + 0.1 mg/kg/day of DRSP and EE, 0.1 to 2 times the exposure (AUC of DRSP) of women taking a contraceptive dose, there was an increase in carcinomas of the harderian gland in the group that received the high dose of DRSP alone. In a similar study in rats given 10 mg/kg/day DRSP alone or 0.3 + 0.003, 3 + 0.03 and 10 + 0.1 mg/kg/day DRSP and EE, 0.8 to
10 times the exposure of women taking a contraceptive dose, there was an increased incidence of benign and total (benign and malignant) adrenal gland pheochromocytomas in the group receiving the high dose of DRSP. Mutagenesis studies for DRSP were conducted in vivo and in vitro and no evidence of mutagenic activity was observed.

14 CLINICAL STUDIES

In the clinical efficacy studies of up to 2 years duration, 2,629 subjects completed 33,160 cycles of use without any other contraception. The mean age of the subjects was 25.5 ± 4.7 years. The age range was 16 to 37 years. The racial demographic was: 83% Caucasian, 1% Hispanic, 1% Black, <1% Asian, <1% other, <1% missing data, 14% not inquired and <1% unspecified. Pregnancy rates in the clinical trials were less than one per 100 woman-years of use.

15 REFERENCES

1. Dinger JC, Heinemann LAJ, et al: The safety of a drospirenone-containing oral contraceptive: final results from the European active surveillance study on oral contraceptives based on 142,475 women-years of observation. Contraception 2007;75:344-354.

2. Seeger JD, Loughlin J, Eng PM, et al: Risk of thromboembolism in women taking ethinyl estradiol/drospirenone and other oral contraceptives. Obstetrics & Gynecology 2007;110(3):587-593.

3. van Hylckama Vlieg A, Helmerhorst FM, Vandenbroucke JP, et al: The venous thrombotic risk of oral contraceptives, effects of oestrogen dose and progestogen type: results of the MEGA case-control study. BMJ 2009;339:b2921.

4. Lidegaard O, Lokkegaard E, Svendsen AL, et al: Hormonal contraception and risk of venous thromboembolism: national follow-up study. BMJ 2009; 339:b2890.

16 HOW SUPPLIED/STORAGE AND HANDLING

16.1 How Supplied

Yasmin (drospirenone/ethinyl estradiol) tablets are available in blister packs (54868-4590-0).

The film-coated tablets are rounded with biconvex faces, one side is embossed with a regular hexagon shape with DO or DP.

Each blister pack contains 28 film-coated tablets in the following order:

21 round, biconvex, yellow, film-coated tablets with embossed “DO” in a regular hexagon on one side each containing 3 mg drospirenone and 0.03 mg ethinyl estradiol
7 round, biconvex, white, film-coated tablets with embossed “DP” in a regular hexagon on one side

16.2 Storage

Store at 25°C (77°F); excursions permitted to 15-30°C (59-86°F) [see USP Controlled Room Temperature].

17 PATIENT COUNSELING INFORMATION

See “FDA-approved patient labeling (Patient Information).”

- Counsel patients that cigarette smoking increases the risk of serious cardiovascular events from COC use, and that women who are over 35 years old and smoke should not use COCs.
- Counsel patients that the increased risk of VTE compared to non-users of COCs is greatest after initially starting a COC or restarting (following a 4-week or greater pill-free interval) the same or a different COC.
- Counsel patients that Yasmin does not protect against HIV infection (AIDS) and other sexually transmitted diseases.
- Counsel patients on Warnings and Precautions associated with COCs.
- Counsel patients that Yasmin contains DRSP. Drospirenone may increase potassium. Patients should be advised to inform their healthcare provider if they have kidney, liver or adrenal disease because the use of Yasmin in the presence of these conditions could cause serious heart and health problems. They should also inform their healthcare provider if they are currently on daily, long-term treatment (NSAIDs, potassium-sparing diuretics, potassium supplementation, ACE inhibitors, angiotensin-II receptor antagonists, heparin or aldosterone antagonists) for a chronic condition.
- Inform patients that Yasmin is not indicated during pregnancy. If pregnancy occurs during treatment with Yasmin, instruct the patient to stop further intake.
- Counsel patients to take one tablet daily by mouth at the same time every day. Instruct patients what to do in the event pills are missed. See “What to Do if You Miss Pills” section in FDA-Approved Patient Labeling.
- Counsel patients to use a back-up or alternative method of contraception when enzyme inducers are used with COCs.
- Counsel patients who are breastfeeding or who desire to breastfeed that COCs may reduce breast milk production. This is less likely to occur if breastfeeding is well established.
- Counsel any patient who starts COCs postpartum, and who has not yet had a period, to use an additional method of contraception until she has taken a yellow tablet for 7 consecutive days.

- Counsel patients that amenorrhea may occur. Rule out pregnancy in the event of amenorrhea in two or more consecutive cycles.

Manufactured for Bayer HealthCare Pharmaceuticals Inc.

Wayne, NJ 07470

Manufactured in Germany

©2012 Bayer HealthCare Pharmaceuticals Inc. All Rights Reserved

Bayer HealthCare Pharmaceuticals Inc.

Additional barcode labeling by:
Physicians Total Care, Inc.
Tulsa, Oklahoma 74146

PACKAGE/LABEL PRINCIPAL DISPLAY PANEL

PLACE DAY LABEL HERE

START

YASMIN® 28

3 MG/0.03 MG

(DROSPIRENONE & ETHINYL ESTRADIOL TABLETS)

Package/Label Principal Display Panel

NDC 54868-4590-0

1 Unit

YASMIN

(drospirenone and ethinyl estradiol tablets) 3 mg/0.03 mg

This product (like all oral contraceptives) is

intended to prevent pregnancy. It does not

protect against HIV infection (AIDS) and other

sexually transmitted diseases.

Store at 25°C with excursions permitted between

15–30°C. [See USP Controlled Room Temperature].

To the Dispenser: This unit contains two pieces of

information intended for the patient, which are

combined in a single booklet. This informational

piece is to be provided to the patient with each

prescription.

Rx only